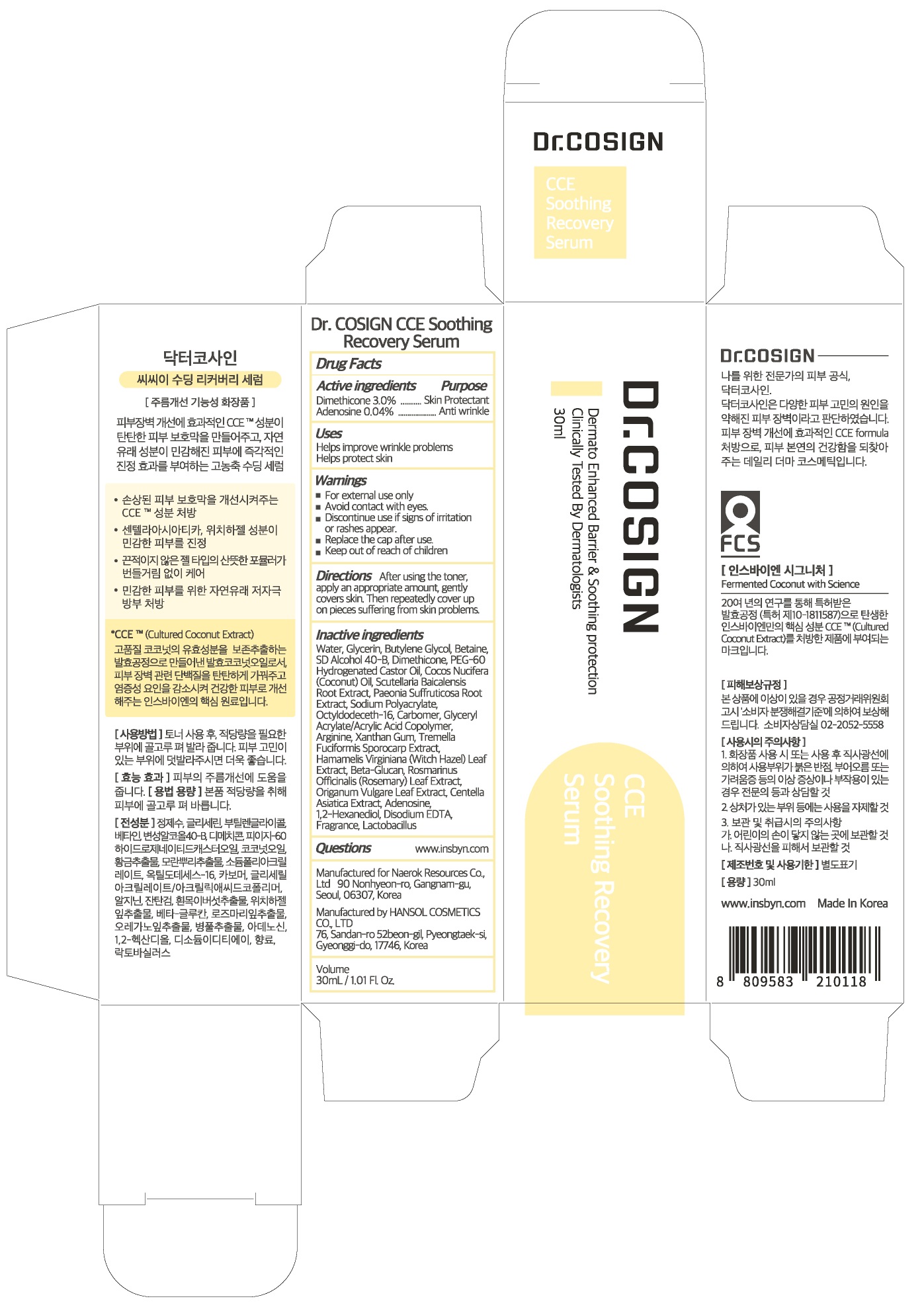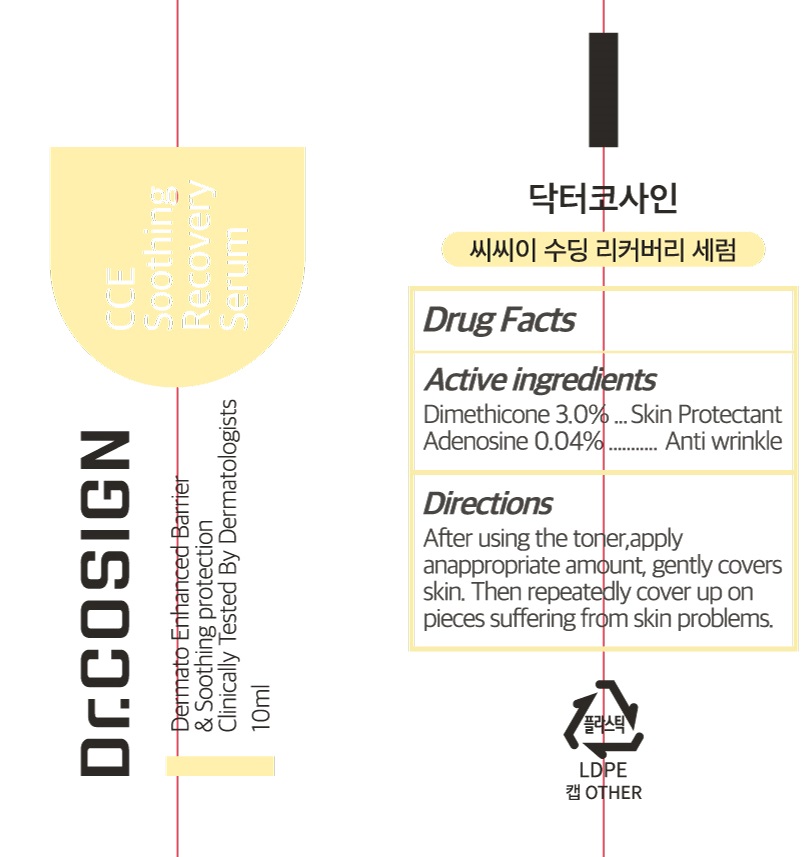 DRUG LABEL: Dr COSIGN CCE Soothing Recovery Serum
NDC: 72642-030 | Form: CREAM
Manufacturer: Naerok Resources Co., Ltd
Category: otc | Type: HUMAN OTC DRUG LABEL
Date: 20181106

ACTIVE INGREDIENTS: Dimethicone 3.0 g/100 mL; Adenosine 0.04 g/100 mL
INACTIVE INGREDIENTS: Water; Glycerin

ACTIVE INGREDIENT

Active ingredients: Dimethicone 3.0%, Adenosine 0.04%

INACTIVE INGREDIENT

Inactive ingredients:

Water, Glycerin, Butylene Glycol, Betaine, SD Alcohol 40-B, PEG-60 Hydrogenated Castor Oil, Cocos Nucifera (Coconut) Oil, Scutellaria Baicalensis Root Extract, Paeonia Suffruticosa Root Extract, Sodium Polyacrylate, Octyldodeceth-16, Carbomer, Glyceryl Acrylate/Acrylic Acid Copolymer, Arginine, Xanthan Gum, Tremella Fuciformis Sporocarp Extract, Hamamelis Virginiana (Witch Hazel) Leaf Extract, Beta-Glucan, Rosmarinus Officinalis (Rosemary) Leaf Extract, Origanum Vulgare Leaf Extract, Centella Asiatica Extract, 1,2-Hexanediol, Disodium EDTA, Fragrance,Lactobacillus

PURPOSE

Purpose: Skin Protectant, Anti wrinkle

WARNINGS

For external use only

Avoid contact with eyes.

Discontinue use if signs of irritation or rashes appear.

Replace the cap after use.

Keep out of reach of children

KEEP OUT OF REACH OF CHILDREN

Uses

Helps improve wrinkle problems

Helps protect skin

Directions

After using the toner, apply an appropriate amount, gently covers skin. Then repeatedly cover up on pieces suffering from skin problems.